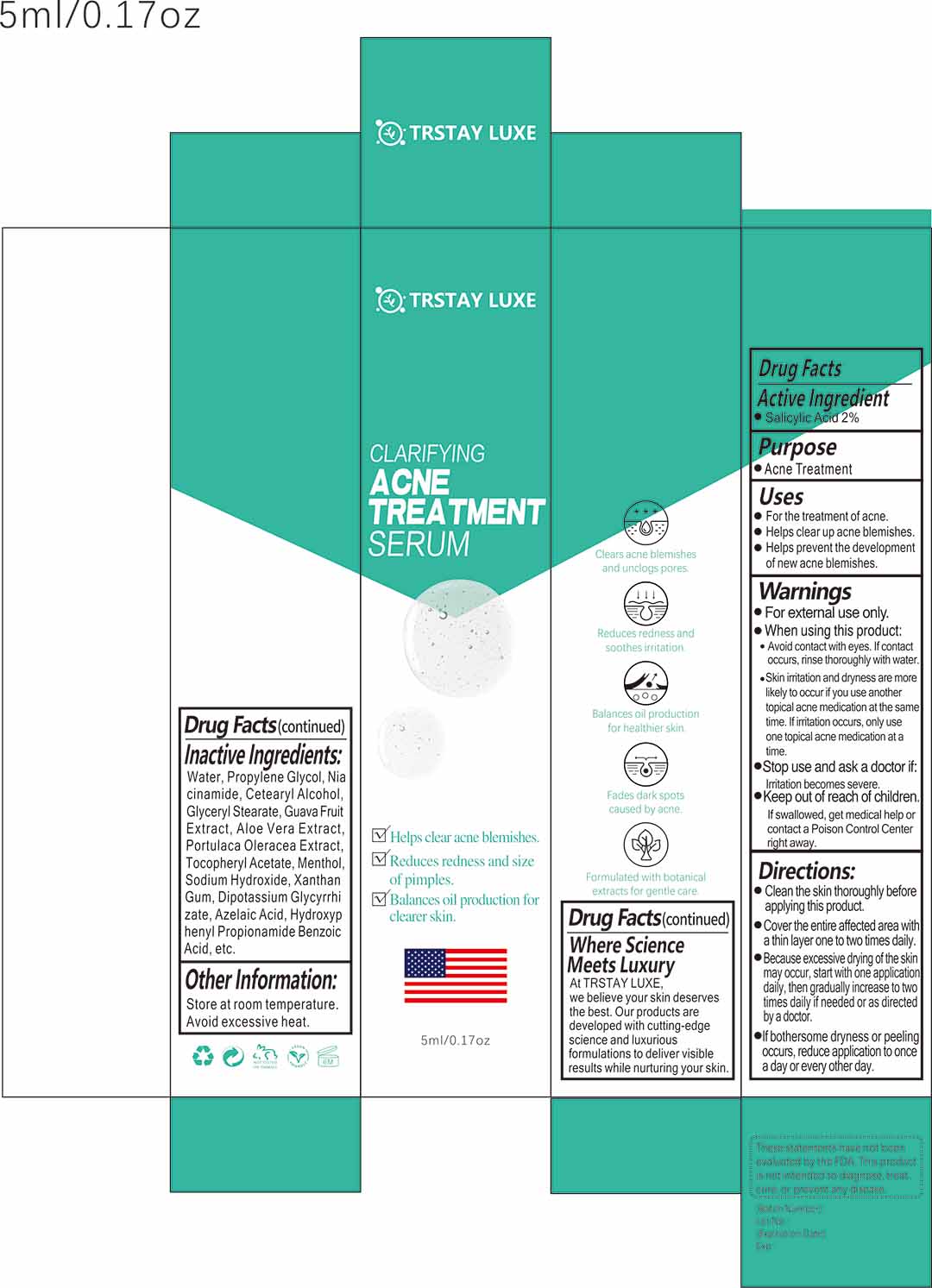 DRUG LABEL: TRSTAY LUXE Clarifying Acne Repair Serum
NDC: 85277-001 | Form: GEL
Manufacturer: Guangdong Meizhiyuan Biotechnology Co., Ltd.
Category: otc | Type: HUMAN OTC DRUG LABEL
Date: 20250219

ACTIVE INGREDIENTS: SALICYLIC ACID 0.02 g/1 mL
INACTIVE INGREDIENTS: WATER; PROPYLENE GLYCOL; PSIDIUM GUAJAVA FRUIT; PURSLANE; AZELAIC ACID; .ALPHA.-TOCOPHEROL ACETATE; SODIUM HYDROXIDE; NIACINAMIDE; ALOE VERA LEAF; XANTHAN GUM; DIPOTASSIUM GLYCYRRHIZATE; MENTHOL

TRSTAY LUXE Clarifying Acne Repair Serum

TRSTAY LUXE Clarifying Acne Repair Serum

ACTIVE INGREDIENT

Salicylic Acid 2%

PURPOSE

Acne Treatment

INDICATIONS AND USAGE

For the treatment of acne.
Helps clear up acne blemishes.
Helps prevent the developmentof new acne blemishes.

WARNINGS

For external use only.

WHEN USING

Avoid contact with eyes. lf contactoccurs, rinse thoroughly with water.
Skin irritation and dryness are morelikely to occur if you use anothertopical acne medication at the sametime. lf irritation occurs, only useone topical acne medication at atime.

Stop use and ask a doctor if:lrritation becomes severe.

Keep out of reach of children.If swallowed, get medical help orcontact a Poison Control Centerright away.

DOSAGE AND ADMINISTRATION

Clean the skin thoroughly beforeapplying this product.
Cover the entire affected area witha thin layer one to two times daily.
Because excessive drying of the skinmay occur, start with one applicationdaily, then gradually increase to twotimes daily if needed or as directedby a doctor.
If bothersome dryness or peelingoccurs, reduce application to oncea day or every other day.

STORAGE AND HANDLING

Store at room temperatureAvoid excessive heat.

INACTIVE INGREDIENT

Water
Propylene Glycol
Niacinamide
Guava Fruit Extract
Aloe Vera Extract
Portulaca Oleracea Extract
Tocopheryl Acetate
Aloe Vera Extract
Menthol
Sodium Hydroxide
Xanthan Gum
Dipotassium Glycyrrhizate
Azelaic Acid